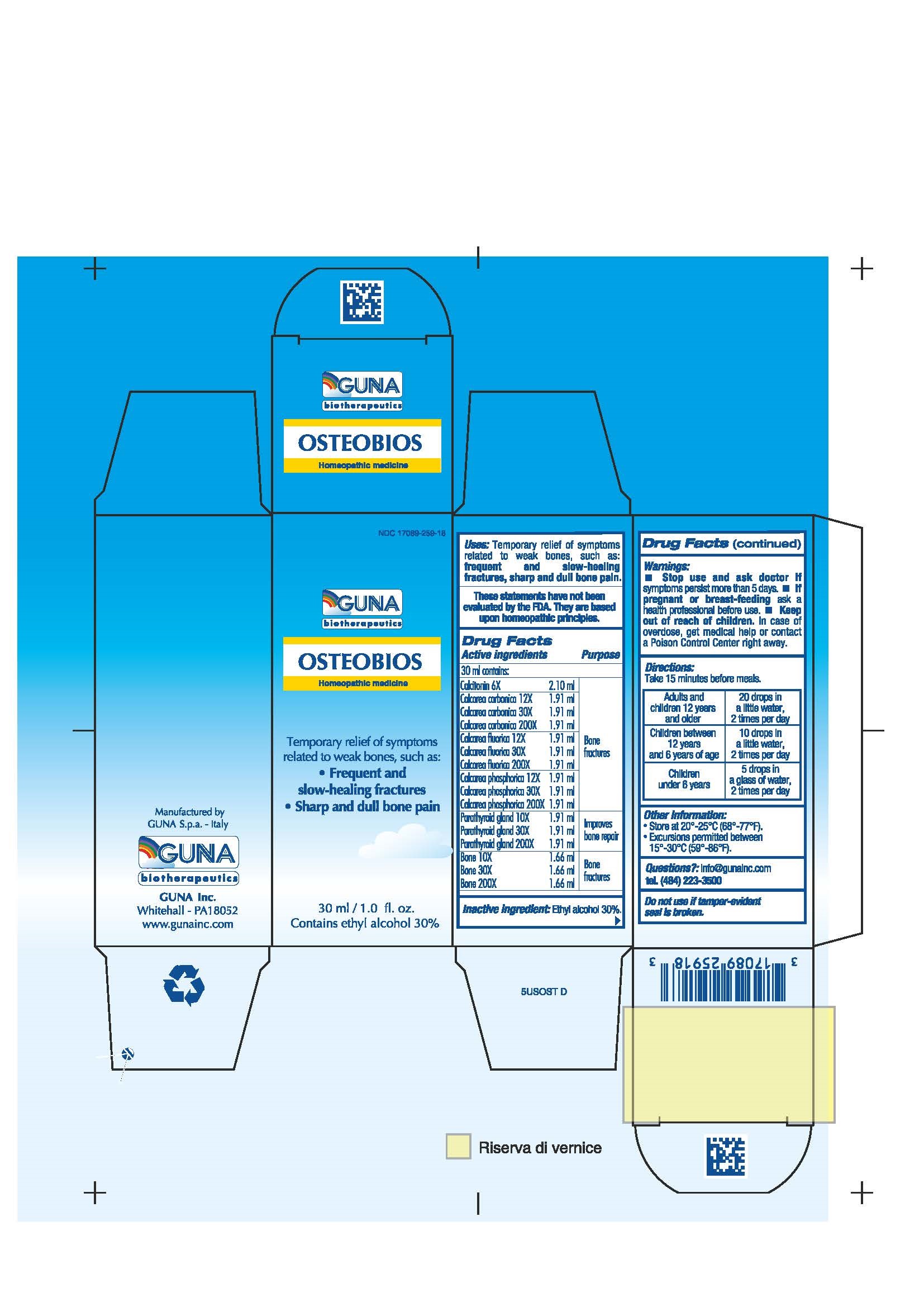 DRUG LABEL: OSTEOBIOS
NDC: 17089-259 | Form: SOLUTION/ DROPS
Manufacturer: Guna spa
Category: homeopathic | Type: HUMAN OTC DRUG LABEL
Date: 20221114

ACTIVE INGREDIENTS: CALCITONIN HUMAN 6 [hp_X]/30 mL; ISOLEUCINE 3 [hp_X]/30 mL; LEUCINE 3 [hp_X]/30 mL; LYSINE 3 [hp_X]/30 mL; METHIONINE 3 [hp_X]/30 mL; PHENYLALANINE 3 [hp_X]/30 mL; THREONINE 3 [hp_X]/30 mL; TRYPTOPHAN 3 [hp_X]/30 mL; VALINE 3 [hp_X]/30 mL; CALCIUM CARBONATE 30 [hp_X]/30 mL; CALCIUM FLUORIDE 30 [hp_X]/30 mL; CALCIUM PHOSPHATE 30 [hp_X]/30 mL; SUS SCROFA BONE 30 [hp_X]/30 mL; SUS SCROFA PARATHYROID GLAND 30 [hp_X]/30 mL
INACTIVE INGREDIENTS: ALCOHOL 9 mL/30 mL

OSTEOBIOS

ACTIVE INGREDIENTS/PURPOSE

BONE 10X 30X 200X BONE FRACTURES
CALCAREA FLUORICA 12X 30X 200X BONE FRACTURES
CALCAREA CARBONICA 12X 30X 200X BONE FRACTURES
CALCAREA PHOSPHORICA 12X 30X 200X BONE FRACTURES
CALCITONIN 6X BONE FRACTURES
PARATHYROID GLAND 10X 30X 200X IMPROVES BONE REPAIR

USES

Temporary relief of symptoms related weak bones such as:

- Frequent and slow-healing fractures
- Sharp and dull bone pain

WARNINGS

Stop use and ask doctor if symptoms persist more than 5 days.
If pregnant or breast-feeding ask a health professional before use.
Keep out of reach of children. In case of overdose, get medical help or contact a Poison Control Center right away.
Contains ethyl alcohol 30%

PREGNANCY

If pregnant or breast-feeding ask a doctor before use

WARNINGS

Keep out of reach of children

DIRECTIONS

Adults and children 12 years and older 20 drops in a little water, 2 times per day
Children between 12 years and 6 years of age 10 drops in a little water, 2 times per day
Children under 6 years 5 drops in a glass of water, 2 times per day

QUESTIONS

Questions?: info@gunainc.com, tel. (484) 223-3500

Inactive ingredient: Ethyl alcohol 30%.

INDICATIONS AND USAGE

Take 15 minutes before meals